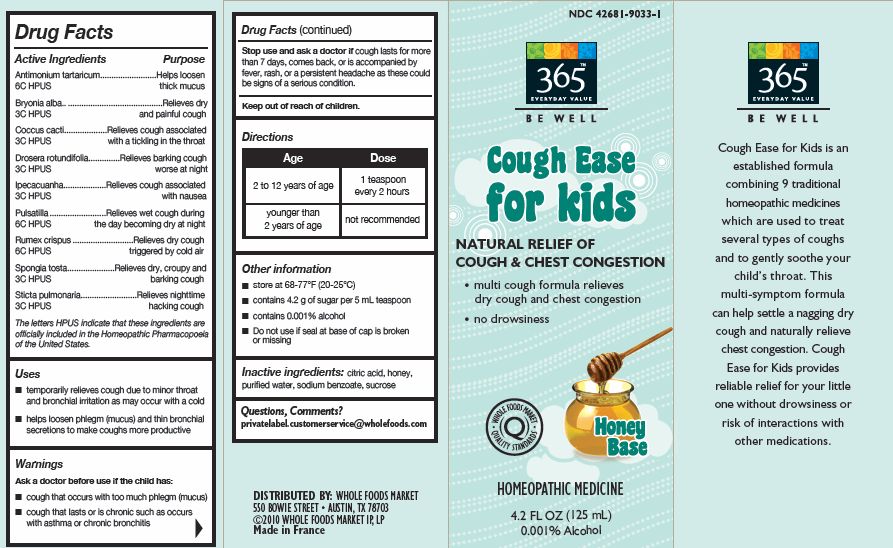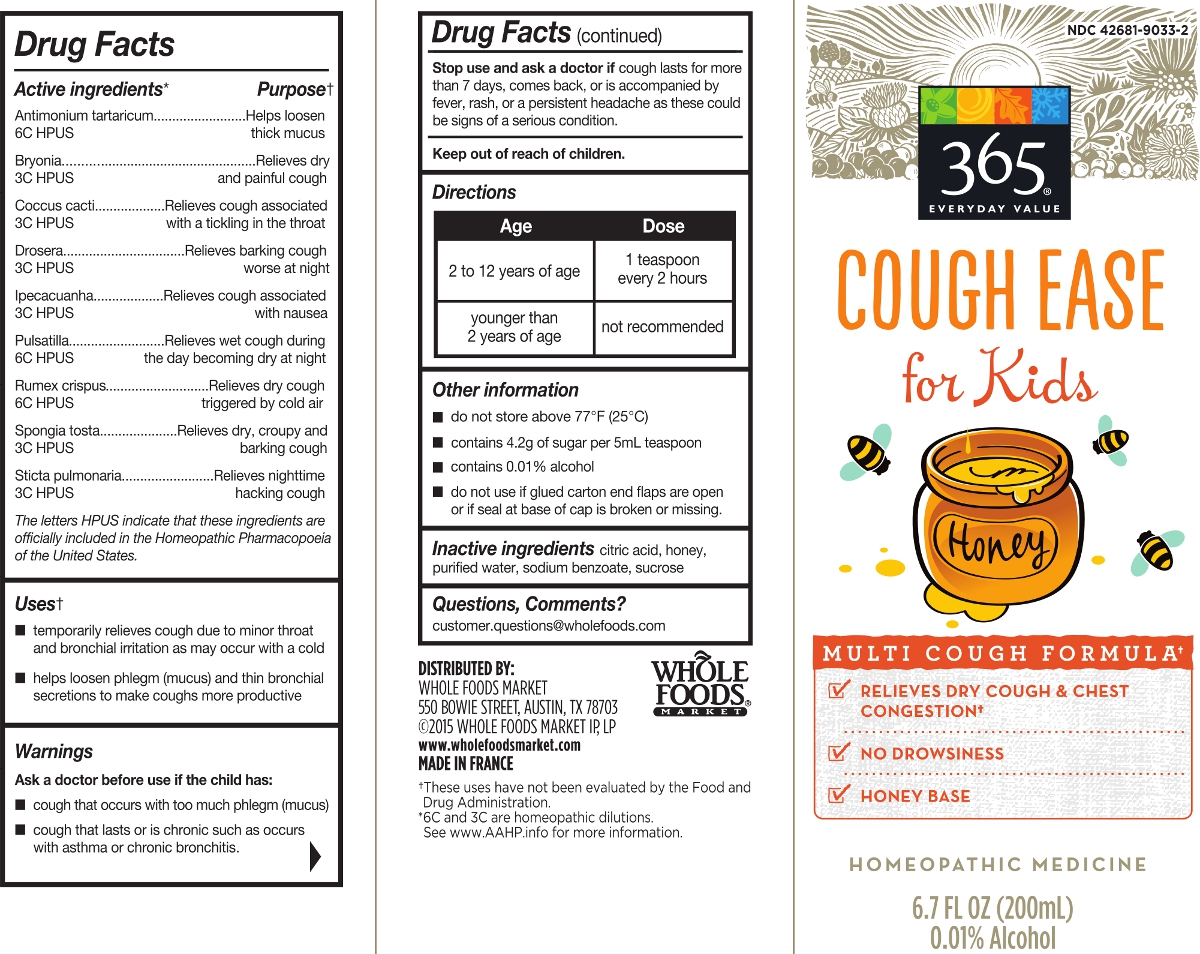 DRUG LABEL: 365 Everyday Value Be Well Cough Ease for Kids
NDC: 42681-9033 | Form: SYRUP
Manufacturer: WFM Private Label, LP
Category: homeopathic | Type: HUMAN OTC DRUG LABEL
Date: 20231004

ACTIVE INGREDIENTS: BRYONIA ALBA ROOT 3 [hp_C]/1 mL; PROTORTONIA CACTI 3 [hp_C]/1 mL; DROSERA ROTUNDIFOLIA 3 [hp_C]/1 mL; IPECAC 3 [hp_C]/1 mL; PULSATILLA VULGARIS 6 [hp_C]/1 mL; RUMEX CRISPUS ROOT 6 [hp_C]/1 mL; SPONGIA OFFICINALIS SKELETON, ROASTED 3 [hp_C]/1 mL; LOBARIA PULMONARIA 3 [hp_C]/1 mL; ANTIMONY POTASSIUM TARTRATE 6 [hp_C]/1 mL
INACTIVE INGREDIENTS: SUCROSE; WATER; CITRIC ACID MONOHYDRATE; SODIUM BENZOATE; HONEY

365 Everyday Value Cough Ease for Kids

ACTIVE INGREDIENT

Antimonium tartaricum 6C
Bryonia alba 3C
Coccus cacti 3C
Drosera rotundifolia 3C
Ipecacuanha 3C
Pulsatilla 6C
Rumex crispus 6C
Spongia tosta 3C
Sticta pulmonaria 3C

INDICATIONS AND USAGE

Temporary relieves cough due to minor throat and bronchial irritation as may occur with a cold.

Helps loosen phlegms (mucus) and thin bronchial secretions to make coughs more productive.

Do not use if seal at base of cap is broken or missing.

DOSAGE AND ADMINISTRATION

Children 2 to 12 years 1 teaspoon every 2 hours

Younger than 2 years of age not recommended

INACTIVE INGREDIENT

citric acid, honey, purified water, sodium benzoate, sucrose

HOW SUPPLIED

200 Ml

PURPOSE

Antimonium tartaricum 6C Helps loosen thick mucus
Bryonia alba 3C Relieves dry and painful cough
Coccus cacti 3C Relieves cough associated with a tickling in the throat
Drosera rotundifolia 3C Relieves barking cough worse at night
Ipecacuanha 3C Relieves cough associated with nausea
Pulsatilla 6C Relieves wet cough during the day becoming worse at night
Rumex crispus 6C Relieves dry cough triggered by cold air
Spongia tosta 3C Relieves dry, croupy and barking cough
Sticta pulmonaria 3C Relieves nighttime hacking cough

STORAGE AND HANDLING

Do not store above 77O F (25O C)

Questions, Comments?

customer.question@wholefoods.com

Ask a doctor before use if he child has

Cough that occurs with too much phlegm (mucus)

Cough that last or is chronic such as occurs with asthma or chronic bronchitis.

Stop use and ask a doctor if cough lasts for more than 7 days, comes back, or is accompanied by fever, rash, or a persistent headache. These could be a sign of a serious condition.

Keep out of reach of children.

Principle Display Panel

Package images